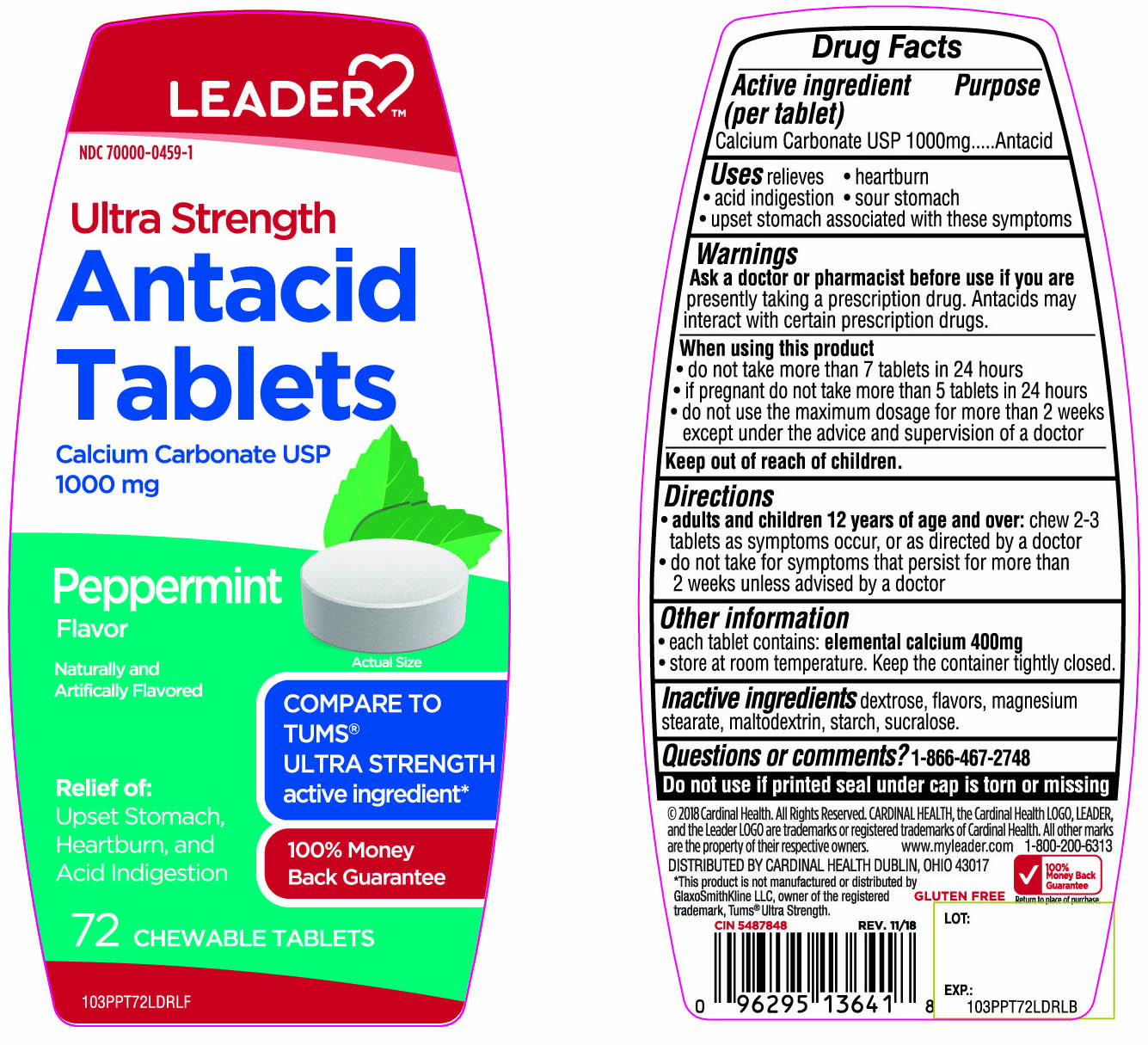 DRUG LABEL: LEADER Ultra Strength
NDC: 70000-0459 | Form: TABLET, CHEWABLE
Manufacturer: Cardinal Health
Category: otc | Type: HUMAN OTC DRUG LABEL
Date: 20260202

ACTIVE INGREDIENTS: CALCIUM CARBONATE 1000 mg/1 1
INACTIVE INGREDIENTS: DEXTROSE, UNSPECIFIED FORM; MAGNESIUM STEARATE; MALTODEXTRIN; STARCH, CORN; SUCRALOSE

Cardinal Ultra Strength Antacid Chewable Tablets

Active ingredient (per tablet)

Calcium Carbonate USP 1000mg

Purpose

Antacid

Uses

relieves

- heartburn
- acid indigestion
- sour stomach
- upset stomach associated with these symptoms

Warnings

Ask a doctor or pharmacist before use if you are presently taking a prescription drug. Antacids may interact with certain prescription drugs.

When using this product

- do not take more than 7 tablets in 24 hours
- if pregnant do not take more than 5 tablets in 24 hours
- do not use the maximum dosage for more than 2 weeks except under the advice and supervision of a doctor.

Directions

- adults and children 12 years of age and over: chew 2-3 tablets as symptoms occur, or as directed by a doctor
- do not take for symptoms that persist for more than 2 weeks unless advised by a doctor

Other information

- each tablet contains: elemental calcium 400mg
- store at room temperature. Keep container tightly closed.

Inactive ingredients

dextrose, flavors, magnesium stearate, maltodextrin, starch, sucralose.

Questions?

1-866-467-2748

Safety sealed: Do not use if printed seal under cap is torn or missing

Package/Label Principal Display Panel

LEADER™

NDC 70000-0459-1

COMPARE TO TUMS® ULTRA STRENGTH active ingredient*

Ultra Strength

Antacid Tablets

Calcium Carbonate USP 1000mg

Peppermint Flavor

Naturally and Artificially Flavored

Relief of:

Upset stomach

Heartburn

Acid indigestion

100% Money Back Guarantee

72 CHEWABLE TABLETS

GLUTEN- FREE

© 2018 Cardinal Health. All Right Reserved. CARDINAL HEALTH, the Cardinal Health LOGO, LEADER and the Leader LOGO are trademarks or registered trademarks of Cardinal Health. All others marks

are the property of their respective owners.

DISTRIBUTED BY CARDINAL HEALTH DUBLIN, OHIO 43017

www.myleader.com 1-800-200-6313

100% Money Back Guarantee

Return to place of purchase.

*This product is not manufactured or distributed by GlaxoSmithKline, owner of the registered trademark, TUMS® Ultra Strength.